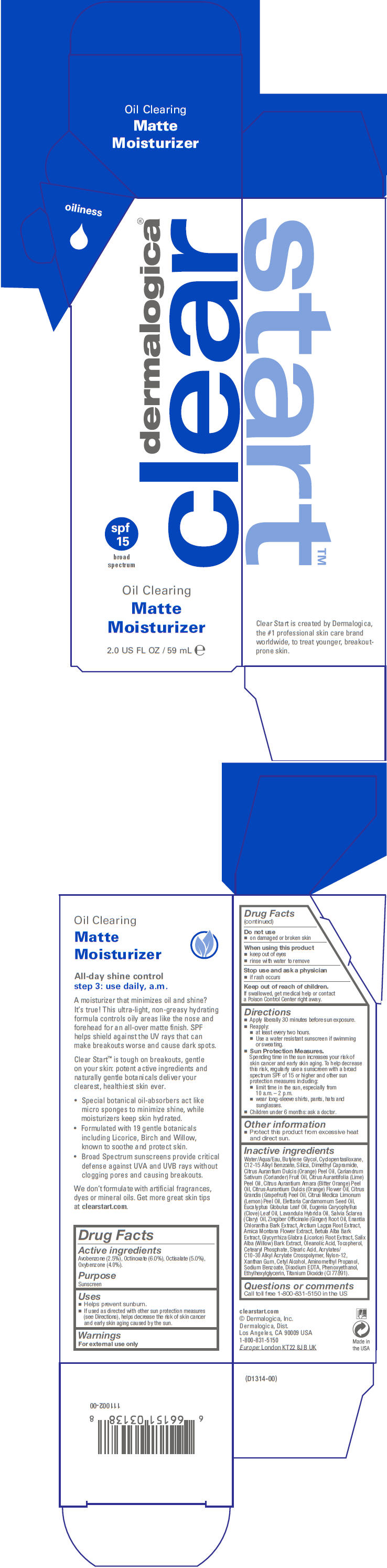 DRUG LABEL: Oil Clearing Matte Moisturizer
NDC: 68479-140 | Form: LOTION
Manufacturer: Dermalogica, Inc.
Category: otc | Type: HUMAN OTC DRUG LABEL
Date: 20140206

ACTIVE INGREDIENTS: Avobenzone 25 mg/1 mL; Octinoxate 60 mg/1 mL; OXYBENZONE 40 mg/1 mL; Octisalate 50 mg/1 mL
INACTIVE INGREDIENTS: Water; Butylene Glycol; Cyclomethicone 5; Alkyl (C12-15) Benzoate; Silicon Dioxide; Dimethyl Capramide; Orange Oil; Coriander Oil; Citrus Aurantiifolia Seed Oil; Bitter Orange Oil; Citrus Sinensis Flower Oil; Citrus Maxima Fruit Rind Oil; Lemon Oil; Cardamom Oil; Eucalyptus Oil; Clove Leaf Oil; Lavandin Oil; Clary Sage Oil; Ginger Oil; Annickia Chlorantha Bark; Arctium Lappa Root; Arnica Montana Flower; Betula Pubescens Bark; Glycyrrhiza Glabra; Salix Alba Bark; Oleanolic Acid; Tocopherol; Stearic Acid; Carbomer Interpolymer Type A (Allyl Sucrose Crosslinked); Nylon-12; Xanthan Gum; Cetyl Alcohol; Aminomethylpropanol; Sodium Benzoate; Edetate Disodium; Ethylhexylglycerin; Phenoxyethanol; Titanium Dioxide

Oil Clearing Matte Moisturizer

Drug Facts

Active ingredients

Avobenzone (2.5%), Octinoxate (6.0%), Octisalate (5.0%), Oxybenzone (4.0%).

Purpose

Sunscreen

Uses

- Helps prevent sunburn.
- If used as directed with other sun protection measures (see Directions), helps decrease the risk of skin cancer and early skin aging caused by the sun.

Warnings

For external use only

Do not use

- on damaged or broken skin

When using this product

- keep out of eyes
- rinse with water to remove

Stop use and ask a physician

- if rash occurs

Keep out of reach of children.
If swallowed, get medical help or contact a Poison Control Center right away.

Directions

- Apply liberally 30 minutes before sun exposure.
- Reapply:
  - at least every two hours.
  - Use a water resistant sunscreen if swimming or sweating.
- Sun Protection Measures.
  Spending time in the sun increases your risk of skin cancer and early skin aging. To help decrease this risk, regularly use a sunscreen with a broad spectrum SPF of 15 or higher and other sun protection measures including:
  - limit time in the sun, especially from 10 a.m. – 2 p.m.
  - wear long-sleeve shirts, pants, hats and sunglasses.
- Children under 6 months: ask a doctor.

Other information

- Protect this product from excessive heat and direct sun.

Inactive ingredients

Water/Aqua/Eau, Butylene Glycol, Cyclopentasiloxane, C12-15 Alkyl Benzoate, Silica, Dimethyl Capramide, Citrus Aurantium Dulcis (Orange) Peel Oil, Cariandrum Sativum (Coriander) Fruit Oil, Citrus Aurantifolia (Lime) Peel Oil, Citrus Aurantium Amara (Bitter Orange) Peel Oil, Citrus Aurantium Dulcis (Orange) Flower Oil, Citrus Grandis (Grapefruit) Peel Oil, Citrus Medica Limonum (Lemon) Peel Oil, Elettaria Cardamomum Seed Oil, Eucalyptus Globulus Leaf Oil, Eugenia Caryophyllus (Clove) Leaf Oil, Lavandula Hybrida Oil, Salvia Sclarea (Clary) Oil, Zingiber Officinale (Ginger) Root Oil, Enantia Chlorantha Bark Extract, Arctium Lappa Root Extract, Arnica Montana Flower Extract, Betula Alba Bark Extract, Glycyrrhiza Glabra (Licorice) Root Extract, Salix Alba (Willow) Bark Extract, Oleanolic Acid, Tocopherol, Cetearyl Phosphate, Stearic Acid, Acrylates/ C10-30 Alkyl Acrylate Crosspolymer, Nylon-12, Xanthan Gum, Cetyl Alcohol, Aminomethyl Propanol, Sodium Benzoate, Disodium EDTA, Phenoxyethanol, Ethylhexylglycerin, Titanium Dioxide (CI 77891).

Questions or comments

Call toll free 1-800-831-5150 in the US

PRINCIPAL DISPLAY PANEL - 59 mL Tube Carton

dermalogica®
clear

spf
15
broad
spectrum

Oil Clearing

Matte
Moisturizer

2.0 US FL OZ / 59 mL e